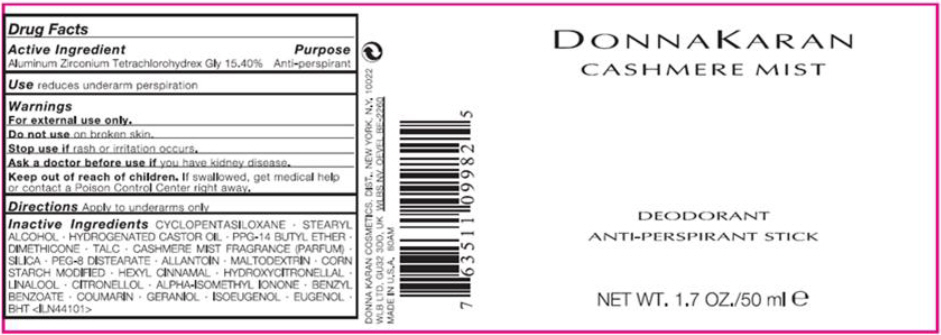 DRUG LABEL: DONNA KARAN CASHMERE MIST DEODORANT ANTI-PERSPIRANT
NDC: 65105-001 | Form: STICK
Manufacturer: DONNA KARAN COSMETICS CO.
Category: otc | Type: HUMAN OTC DRUG LABEL
Date: 20210709

ACTIVE INGREDIENTS: ALUMINUM ZIRCONIUM TETRACHLOROHYDREX GLY 154 mg/1 mL
INACTIVE INGREDIENTS: CYCLOMETHICONE 5; STEARYL ALCOHOL; HYDROGENATED CASTOR OIL; PPG-14 BUTYL ETHER; DIMETHICONE; TALC; SILICON DIOXIDE; PEG-8 DISTEARATE; ALLANTOIN; MALTODEXTRIN; .ALPHA.-HEXYLCINNAMALDEHYDE; HYDROXYCITRONELLAL; LINALOOL, (+/-)-; .BETA.-CITRONELLOL, (R)-; ISOMETHYL-.ALPHA.-IONONE; BENZYL BENZOATE; COUMARIN; GERANIOL; ISOEUGENOL; EUGENOL; BUTYLATED HYDROXYTOLUENE

DONNA KARAN CASHMERE MIST DEODORANT ANTI-PERSPIRANT STICK

Drug Facts

Active Ingredient

Aluminum Zirconium Tetrachlorohydrex Gly 15.40%

Purpose

Anti-perspirant

Use

reduces underarm perspiration

Warnings

For external use only.

Do not use on broken skin.

Stop use if rash or irritation occurs.

Ask a doctor before use if you have kidney disease.

Keep out of reach of children. If swallowed, get medical help or contact a Poison Control Center right away.

Directions

Apply to underams only

Inactive Ingredients

CYCLOPENTASILOXANE • STEARYL ALCOHOL • HYDROGENATED CASTOR OIL • PPG-14 BUTYL ETHER • DIMETHICONE • TALC • CASHMERE MIST FRAGRANCE (PARFUM) • SILICA • PEG-8 DISTEARATE • ALLANTOIN • MALTODEXTRIN • CORN STARCH MODIFIED • HEXYL CINNAMAL • HYDROXYCITRONELLAL • LINALOOL • CITRONELLOL • ALPHA-ISOMETHYL IONONE • BENZYL BENZOATE • COUMARIN • GERANIOL • ISOEUGENOL • EUGENOL • BHT <ILN44101>

PRINCIPAL DISPLAY PANEL - 50 ml Canister Label

DONNA KARAN
CASHMERE MIST

DEODORANT
ANTI-PERSPIRANT STICK

NET WT. 1.7 OZ./50 ml ℮